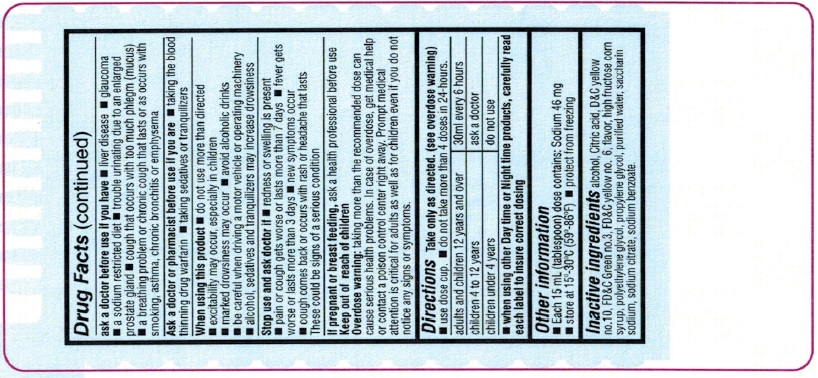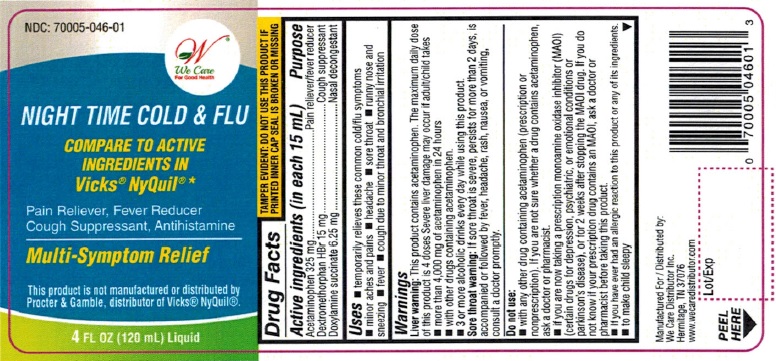 DRUG LABEL: nite time
NDC: 70005-046 | Form: LIQUID
Manufacturer: We Care Distributor Inc.
Category: otc | Type: HUMAN OTC DRUG LABEL
Date: 20160810

ACTIVE INGREDIENTS: ACETAMINOPHEN 325 mg/15 mL; DEXTROMETHORPHAN HYDROBROMIDE 15 mg/15 mL; DOXYLAMINE SUCCINATE 6.25 mg/15 mL
INACTIVE INGREDIENTS: ALCOHOL; ANHYDROUS CITRIC ACID; D&C YELLOW NO. 10; FD&C GREEN NO. 3; FD&C YELLOW NO. 6; HIGH FRUCTOSE CORN SYRUP; POLYETHYLENE GLYCOL; PROPYLENE GLYCOL; WATER; SACCHARIN SODIUM; SODIUM CITRATE; SODIUM BENZOATE

NiteTime Cold and Flu Drug Facts

Active ingredient (in each 15 mL tablespoon)

Acetaminophen 325 mg

Dextromethorphan HBr 15 mg

Doxylamine succinate 6.25 mg

Purpose

Pain reliever/fever reducer

Cough suppressant

Nasal decongestant

Uses

temporarily relieves common cold/flu symptoms:

- minor aches and pains
- headache
- sore throat
- runny nose and sneezing
- fever
- cough due to minor throat and bronchial irritation

Warnings

Liver warning: This product contains acetaminophen. The maximum daily dose of this product is 4 doses. Severe liver damage may occur if adult/child takes:

- more than 4,000 mg of acetaminophen in 24 hours
- with other drugs containing acetaminophen
- 3 or more alcoholic drinks every day while using this product

Sore throat warning: If sore throat is severe, persists for more than two days, is accompanied or followed by fever, headache, rash, nausea, or vomiting, consult a doctor promptly.

Do not use

- with any other drug containing acetaminophen (prescription or nonprescription). If you are not sure whether a drug contains acetaminophen, ask a doctor or pharmacist.
- if you are now taking a prescription monoamine oxidase inhibitor (MAOI) (certain drugs for depression, psychiatric or emotional conditions, or Parkinson’s disease), or for 2 weeks after stopping the MAOI drug. If you do not know if your prescription drug contains an MAOI, ask a doctor or pharmacist before taking this product.
- if you have ever had an allergic reaction to this product or any of its ingredients
- to make a child sleepy

Ask a doctor before use if you have

- liver disease
- glaucoma
- a sodium-restricted diet
- trouble urinating due to an enlarged prostate gland
- cough that occurs with too much phlegm (mucus)
- a breathing problem or chronic cough that lasts or occurs with smoking, asthma chronic bronchitis or emphysema

Ask a doctor or pharmacist before use if you are

- taking the blood thinning drug warfarin
- taking sedatives or tranquilizers

When using this product

- do not use more than directed
- excitability may occur, especially in children
- marked drowsiness may occur
- avoid alcoholic drinks
- be careful when driving a motor vehicle or operating machinery
- alcohol, sedatives and tranquilizers may increase drowsiness

Stop use and ask a doctor if

- redness or swelling is present
- pain or cough gets worse or lasts more than 7 days
- fever gets worse or lasts more than 3 days
- new symptoms occur
- cough comes back or occurs with rash or headache that lasts.

These could be signs of a serious condition.

If pregnant or breast-feeding,

ask a health professional before use.

Keep out of reach of children.

Overdose warning: Taking more than recommended dose may cause serious health problems. In case of overdose, get medical help or contact a Poison Control Center right away. Prompt medical attention is critical for adults as well as for children even if you do not notice any signs or symptoms.

Directions

- take only as directed. (see overdose warning)
- use dose cup
- do not exceed 4 doses per 24 hours

adults and children 12 years and over | 30 mL every 6 hours
children 4 to under 12 years | ask a doctor
children under 4 years | do not use

- when using other Daytime or Nighttime products, carefully read each label to insure correct dosing

Other information

- each 15 mL (tablespoon) contains: sodium 46 mg
- store at 15°-30°C (59°-86°F)
- protect from freezing

Inactive ingredients

alcohol, citric acid, D&C yellow no. 10, FD&C green no. 3, FD&C yellow no. 6, flavor, high fructose corn syrup, polyethylene glycol, propylene glycol, purified water, saccharin sodium, sodium citrate, sodium benzoate

Questions or comments?

1-888-705-WECARE (Mon-Fri 9am-5pm EST) or www.wecaredistributor.com

Principal Display Panel

See New Warnings Information

Compare to NyQuil® Cold & Flu Active Ingredients

NiteTime

Cold & Flu

Pain Reliever, Fever Reducer, Cough Suppressant, Antihistamine

Multi-Symptom Relief

Aches, Fever - Acetaminophen

Cough - Dextromethorphan HBr

Sneezing, Runny Nose - Doxylamine Succinate

Original Flavor

10% Alcohol